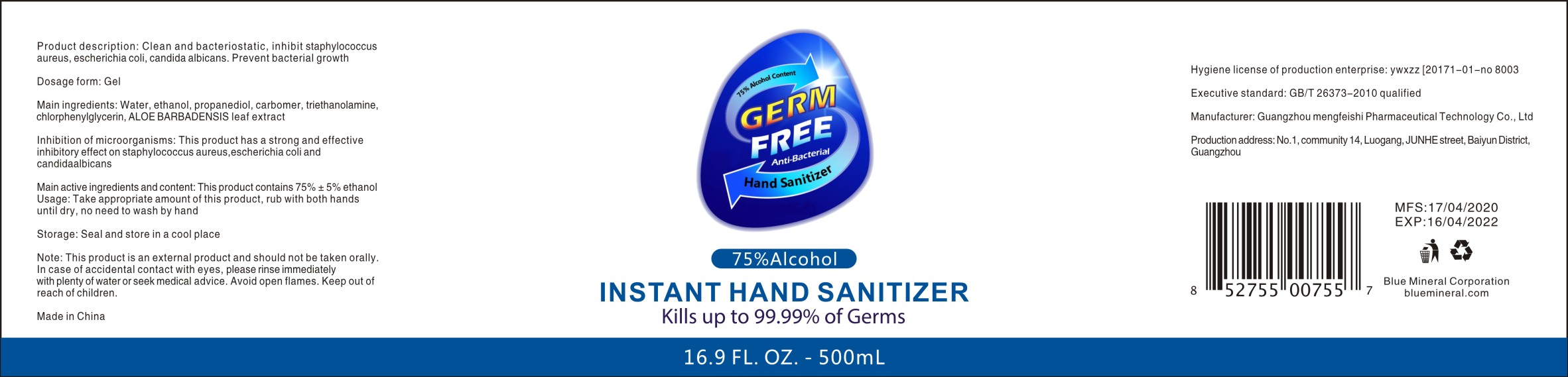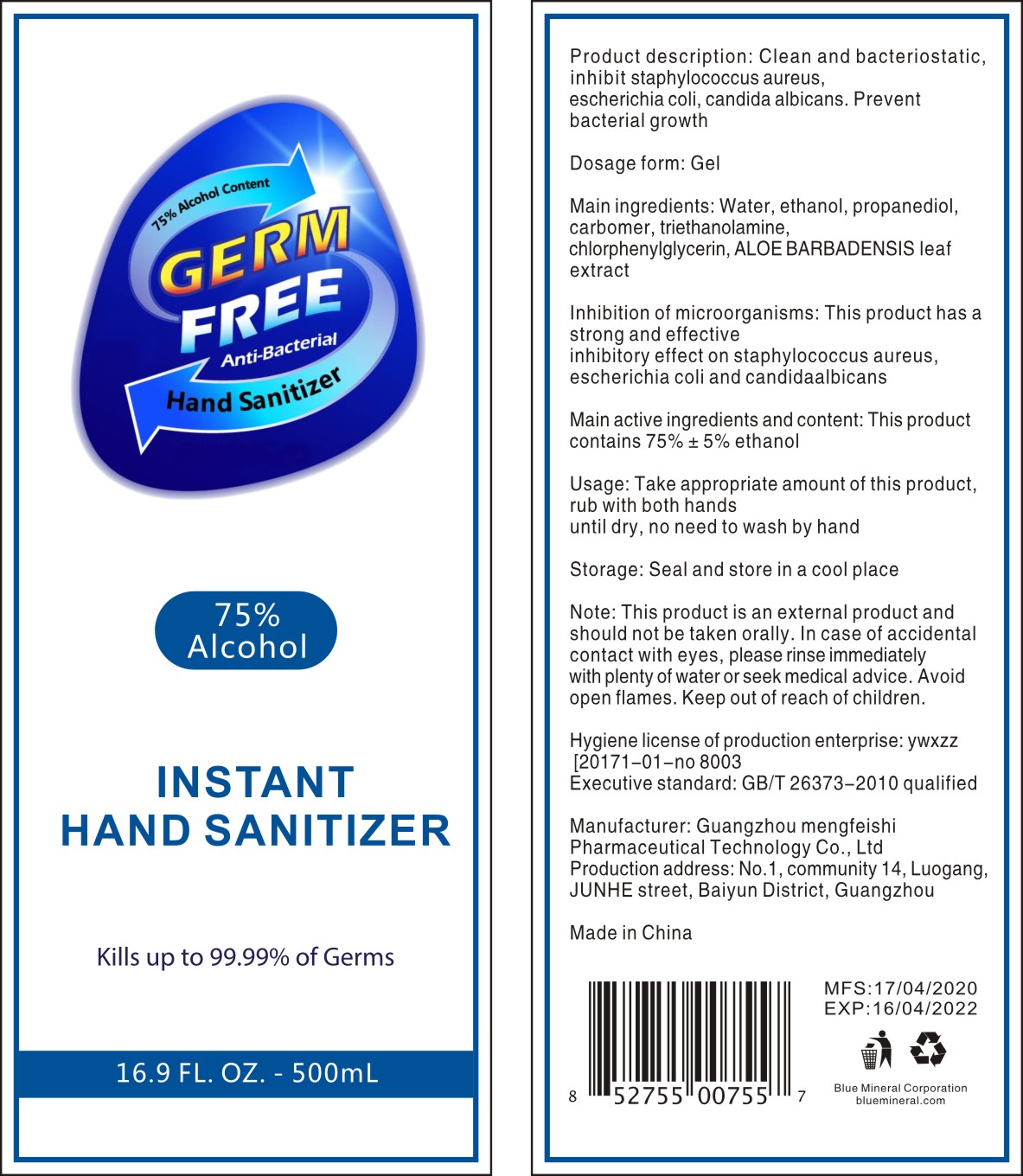 DRUG LABEL: GERM FREE Instant hand sanitizer
NDC: 77311-500 | Form: GEL
Manufacturer: Guangzhou Mengfeishi Pharmaceutical Technology Co., Ltd.
Category: otc | Type: HUMAN OTC DRUG LABEL
Date: 20200522

ACTIVE INGREDIENTS: ALCOHOL 75 mL/100 mL
INACTIVE INGREDIENTS: WATER; ALOE VERA LEAF; PROPANEDIOL; TROLAMINE; CHLORPHENESIN; CARBOMER HOMOPOLYMER, UNSPECIFIED TYPE

Main active ingredients and content

This product contains 75% ± 5% ethanol

Product description

Clean and bacteriostatic, inhibit staphylococcus aureas, escherichia coli, candida albicans. Prevent bacterial growth

Inhibition of microorganisms

This product has a strong and effective inhibitory effect on staphylococcus aureus, escherichia coli and candidaalbicans

Dosage form

Gel

Usage

Take appropriate amount of this product, rub with both hands until dry, no need to wash by hand

Note

This product is an external product and should not be taken orally. In case of accidental contact with eyes, please rinse immediately with plenty of water or seek medical advice. Avoid open flames.

Keep out of reach of children

Main ingredients

Water, ethanol, propanediol, carbomer, triethanolamine, chlorphenylglycerin, ALOE BARBADENSIS leaf extract

Storage

Seal and store in a cool place

Package Label - Principal Display Panel

NDC 77311-500-02

77311-500-03